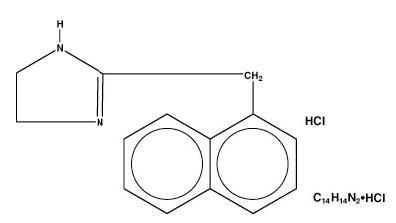 DRUG LABEL: Unknown
Manufacturer: CIBA Vision
Category: prescription | Type: HUMAN PRESCRIPTION DRUG LABELING
Date: 20060831

Vasocon

VASOCON REGULAR

NAPHAZOLINE HYDROCHLORIDE OPHTHALMIC SOLUTION USP, 0.1%

DESCRIPTION

Naphazoline HCl, an ocular vasoconstrictor, is an imidazoline derivative sympathomimetic amine. The active ingredient is represented by the structural formula:

Chemical Name:

2-(1-naphthylmethyl)-2-imidazoline monohydrochloride

VASOCON REGULAR ophthalmic solution is a sterile solution containing 1 mg/mL naphazoline hydrochloride in an isotonic solution containing polyethylene glycol 8000, sodium chloride, polyvinyl alcohol, edetate disodium and purified water; preserved with benzalkonium chloride. Hydrochloric acid and/or sodium hydroxide added to adjust pH. It has a pH of 5.5 to 7.0.

CLINICAL PHARMACOLOGY

Naphazoline constricts the vascular system of the conjunctiva. It is presumed that this effect is due to direct stimulation action of the drug upon the alpha adrenergic receptors in the arterioles of the conjunctiva resulting in decreased conjunctival congestion. Naphalozine belongs to the imidazoline class of sympathomimetics.

INDICATIONS AND USAGE

VASOCON REGULAR is indicated for use as a topical ocular vasoconstrictor.

CONTRAINDICATIONS

Contraindicated in the presence of an anatomically narrow angle or in narrow angle glaucoma or in persons who have shown hypersensitivity to any component of this preparation.

WARNINGS

Patients under therapy with MAO inhibitors may experience a severe hypertensive crisis if given a sympathomimetic drug. Use in children, especially infants, may result in CNS depression leading to coma and marked reduction in body temperature.

PRECAUTIONS

General

Use with caution in the presence of hypertension, cardiovascular abnormalities, hyperglycemia (diabetes), hyperthyroidism, ocular infection or injury and when other medications are being used.

Patient Information

Patients should be advised to discontinue the drug and consult a physician if relief is not obtained within 48 hours of therapy, if irritation, blurring, or redness persists or increases, or if symptoms of systemic absorption occur, i.e., dizziness, headache, nausea, decrease in body temperature, or drowsiness.

To prevent contaminating the dropper tip and solution, do not touch the eyelids or the surrounding area with the dropper tip of the bottle. If solution changes color or becomes cloudy, do not use.

Drug Interactions

Concurrent use of maprotiline or tricyclic antidepressants and naphazoline may potentiate the pressor effect of naphazoline. Patients under therapy with MAO inhibitors may experience a severe hypertensive crisis if given a sympathomimetic drug. (See WARNINGS).

Pregnancy Category C

Animal reproduction studies have not been conducted with naphazoline. It is also not known whether naphazoline can cause fetal harm when administered to a pregnant woman or can affect reproduction capacity. Naphazoline should be given to a pregnant woman only if clearly needed.

Nursing Mothers

If is not known whether naphazoline is excreted in human milk. Because many drugs are excreted in human milk, caution should be exercised when naphazoline is administered to a nursing woman.

Pediatric Use

Safety and effectiveness in children have not been established. See “WARNINGS” and “CONTRAINDICATIONS”.

ADVERSE REACTIONS

Ocular

Mydriasis, increased redness, irritation, discomfort, blurring, punctate keratitis, lacrimation, increased intraocular pressure.

Systemic

Dizziness, headache, nausea, sweating, nervousness drowsiness, weakness, hypertension, cardiac irregularities, and hyperglycemia.

DOSAGE AND ADMINISTRATION

Instill one or two drops in the conjunctival sac(s) every three to four hours as needed.

HOW SUPPLIED

VASOCON REGULAR (naphazoline hydrochloride ophthalmic solution USP, 0.1%): 15 mL plastic squeeze bottle with dropper tip. NDC 58768-844-15 To be dispensed only in original, unopened container. Store at controlled room temperature 15°-30°C (59°-86°F).

CAUTION: Federal law prohibits dispensing without prescription.

Mfd. by OMJ Pharmaceuticals, Inc.,

San Germán, P.R., 00683 for:

CIBA Vision

Ophthalmics®

___________________

Atlanta, Georgia 30155

6072-A